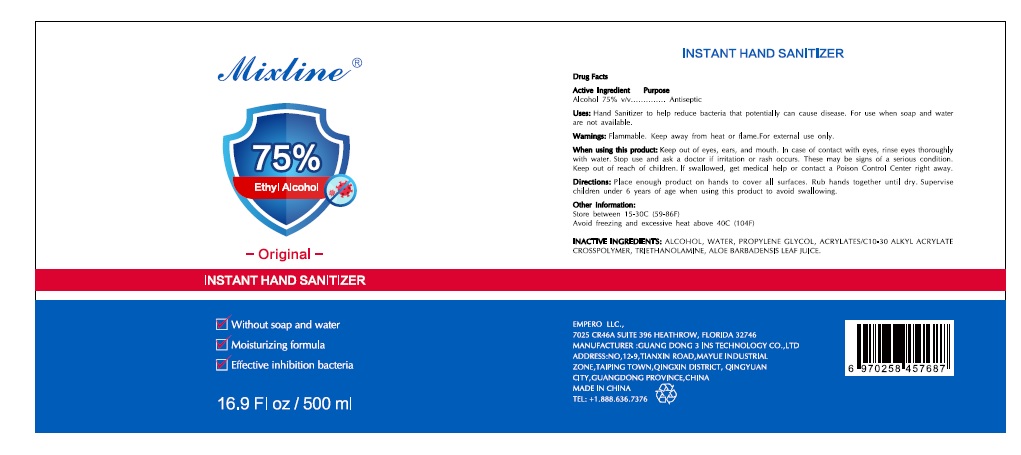 DRUG LABEL: Mixline
NDC: 76778-075 | Form: SOLUTION
Manufacturer: EMPERO LLC
Category: otc | Type: HUMAN OTC DRUG LABEL
Date: 20200428

ACTIVE INGREDIENTS: ALCOHOL 75 mL/100 mL
INACTIVE INGREDIENTS: WATER; PROPYLENE GLYCOL; CARBOMER INTERPOLYMER TYPE A (ALLYL SUCROSE CROSSLINKED); TROLAMINE; ALOE VERA LEAF

Active Ingredient

Alcohol 75% v/v

Purpose

Antiseptic

Uses

Hand Sanitizer to help reduce bacteria that potentially can cause disease. For use when soap and water are not available.

Warnings

Flammable. Keep away from heat or flame. For external use only.

When using this product

Keep out of eyes, ears, and mouth. In case of contact with eyes, rinse eyes thoroughly with water.
Stop use and ask a doctor if irritation or rash occurs. These may be signs of a serious condition.

Keep out of reach of children.

If swallowed, get medical help or contact a Poison Control Center right away.

Directions

- Place enough product on hands to cover all surfaces. Rub hands together until dry.
- Supervise children under 6 years of age when using this product to avoid swallowing.

Other information

- Store between 15-30C (59-86F)
- Avoid freezing and excessive heat above 40C (104F)

Inactive ingredients

Alcohol, Water, Propylene Glycol, Acrylates/C10-30 Alkyl Acrylate Crosspolymer, Triethanolamine, Aloe Barbadensis Leaf Juice.

Principal Display Panel

NDC 76778-075-17

Mixline 75% Ethyl Alcohol

Original

INSTANT HAND SANITIZER

- Without soap and water
- Moisturizing formula
- Effective inhibition bacteria

16.9 Fl oz/ 500 ml